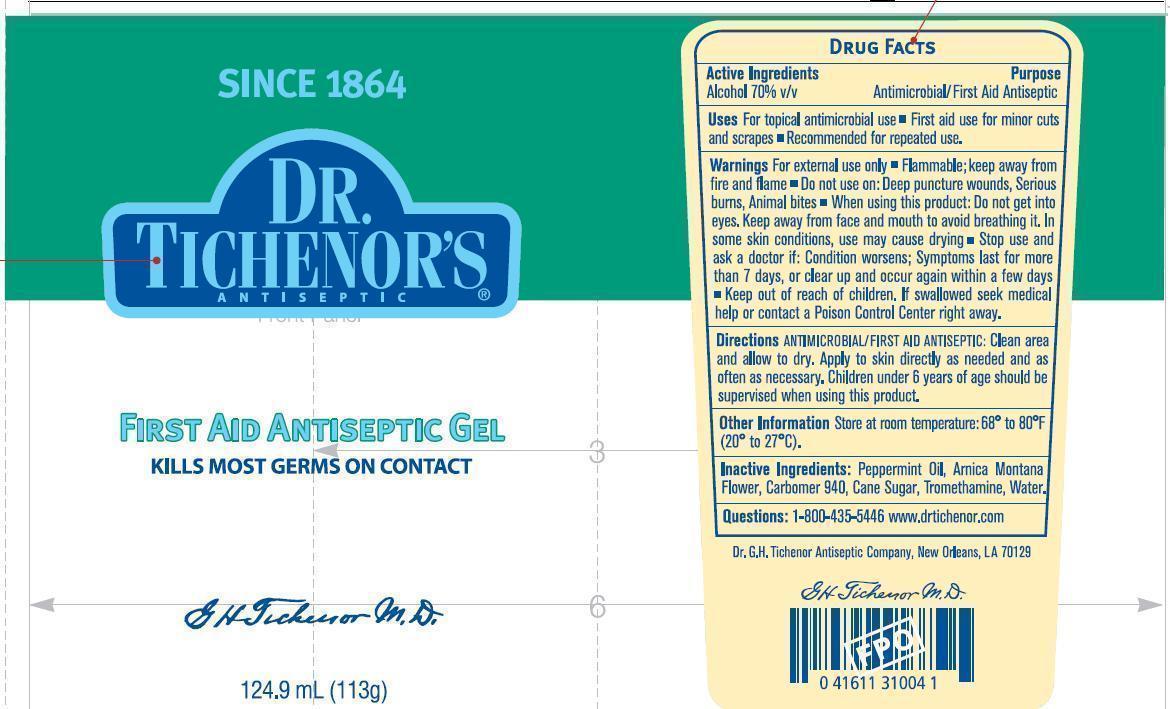 DRUG LABEL: Dr Tichenors
NDC: 11291-070 | Form: GEL
Manufacturer: Dr. G. H. Tichenor's Antiseptic Company
Category: otc | Type: HUMAN OTC DRUG LABEL
Date: 20250109

ACTIVE INGREDIENTS: ALCOHOL 7 mL/10 mL
INACTIVE INGREDIENTS: PEPPERMINT OIL; ARNICA MONTANA FLOWER; CARBOMER HOMOPOLYMER TYPE C (ALLYL PENTAERYTHRITOL CROSSLINKED); SUGARCANE; TROMETHAMINE; WATER

Dr. Tichenor's First Aid Antiseptic Gel - Drug Facts Label

Active Ingredients

Alcohol 70% v/v

Purpose

Antimicrobial/First Aid Antiseptic

Uses

- For topical antimicrobial use
- First aid use for minor cuts and scrapes
- Recommended for repeated use.

Warnings

- For external use only
- Flammable; keep away from fire and flame

Do not use on: Deep puncture wounds, Serious burns, Animal bites

When using this product: Do not get into eyes. Keep away from face and mouth to avoid breathing it. In some conditions, use may cause drying

Stop use and ask a doctor if: Condition worsens; Symptoms last for more than 7 days, or clear up and occur again within a few days

Keep out of reach of children. If swallowed seek medical help or contact a Poison Control Center right away.

Directions

ANTIMICROBIAL/FIRST AID ANTISEPTIC: Clean area and allow to dry. Apply to skin directly as needed and as often as necessary. Children under 6 years of age should be supervised when using this product.

Other Information

Store at room temperature: 68º to 80ºF (20º to 27ºC).

Inactive Ingredients:

Peppermint Oil, Arnica Montana Flower, Carbomer 940, Cane Sugar, Tromethamine, Water.

Questions:

1-800-435-5446 www.drtichenor.com

Image of Label

DrTichenorAntisepticGelLabel.jpg